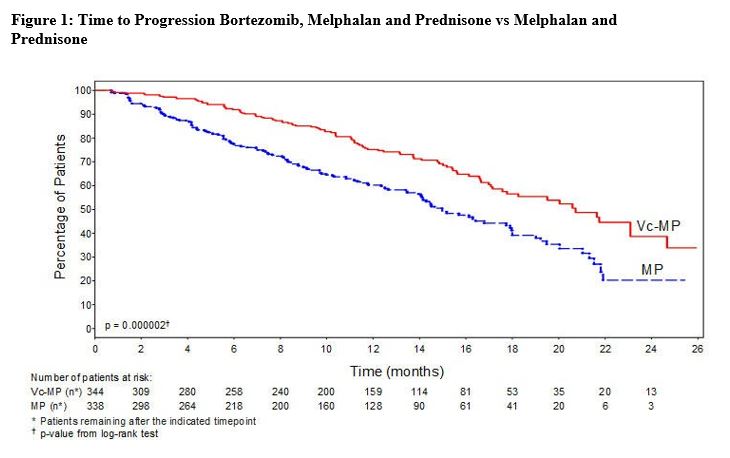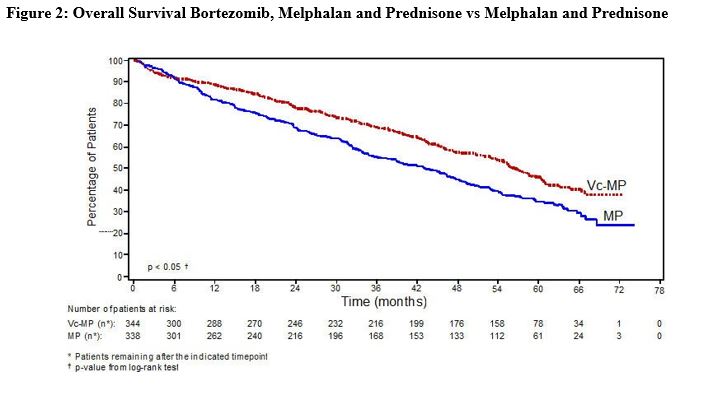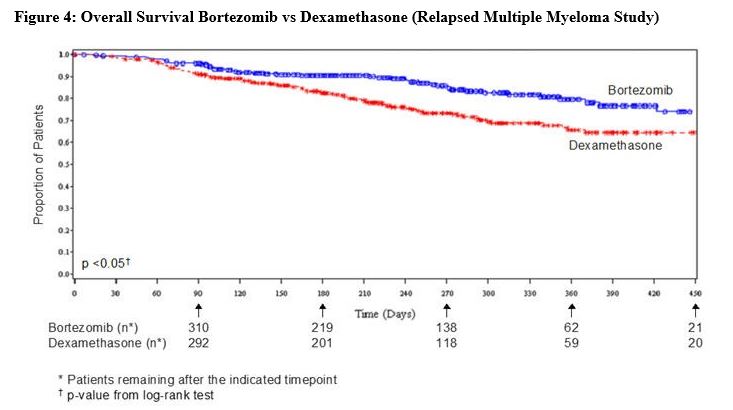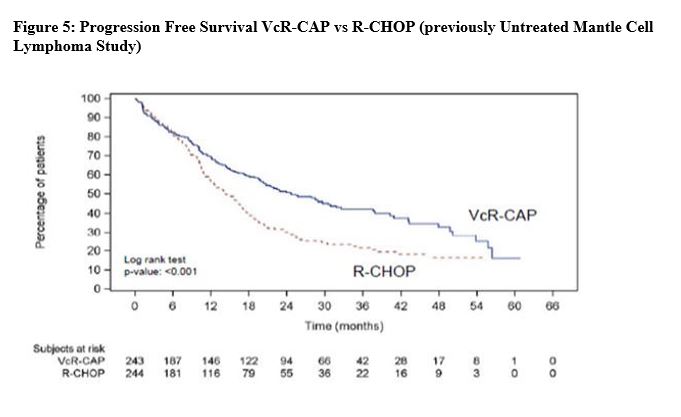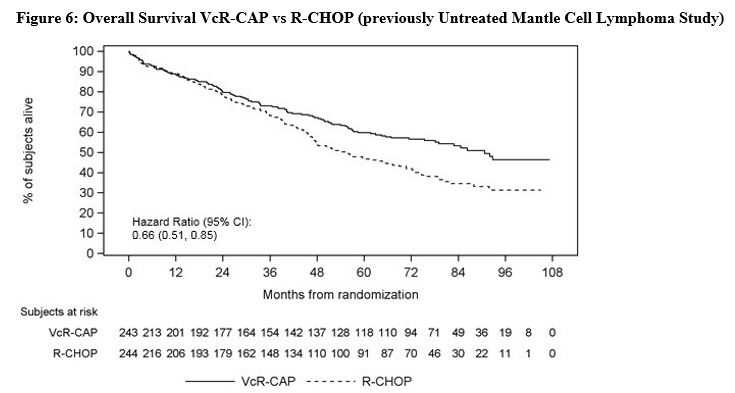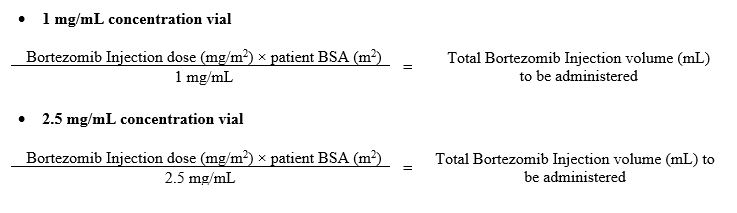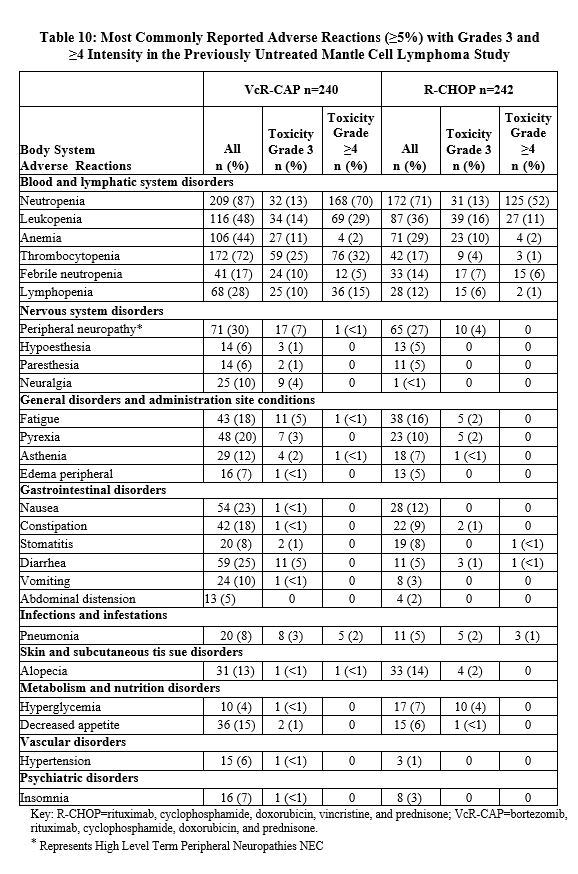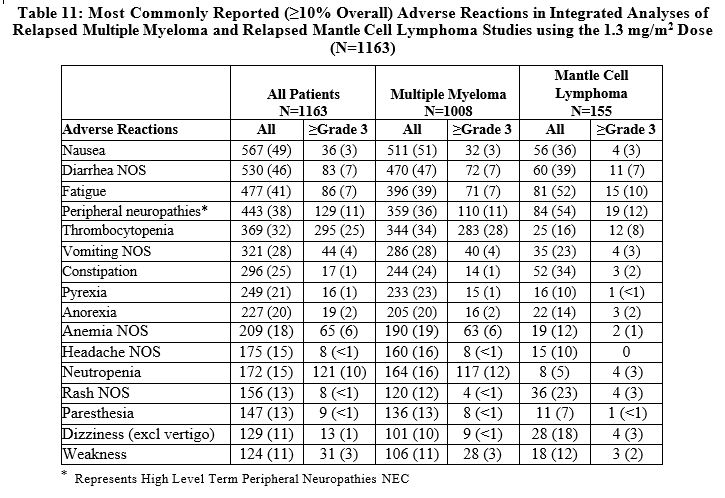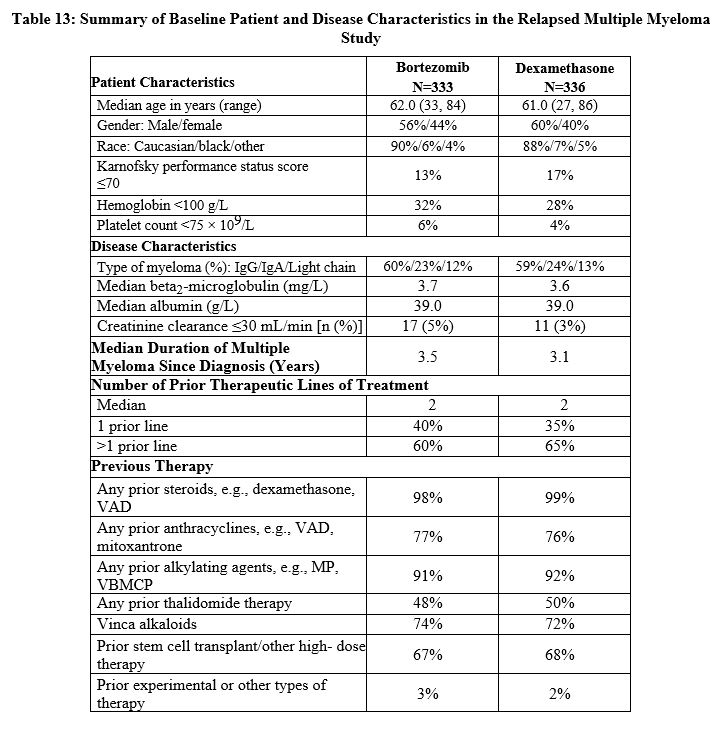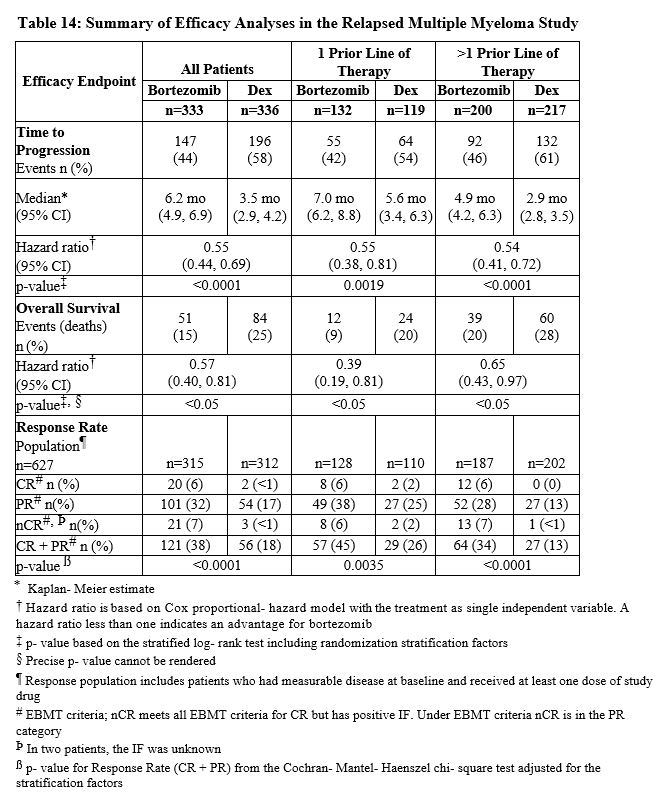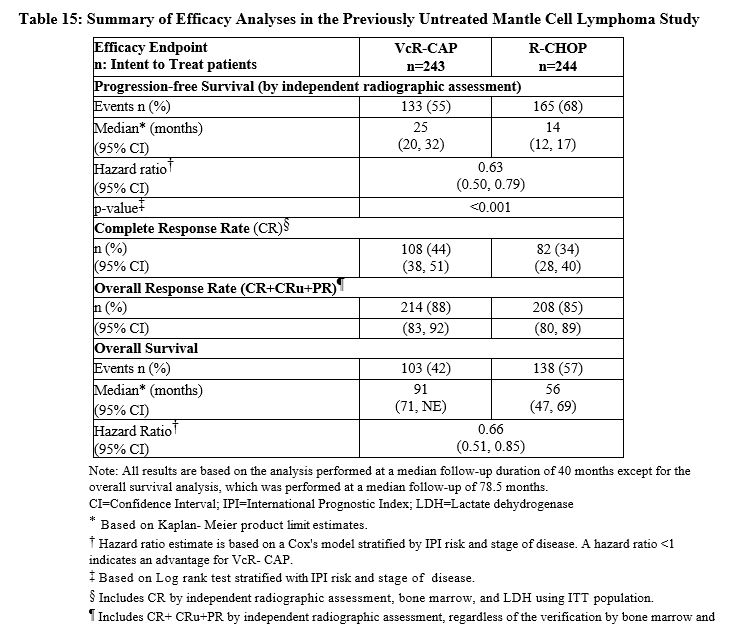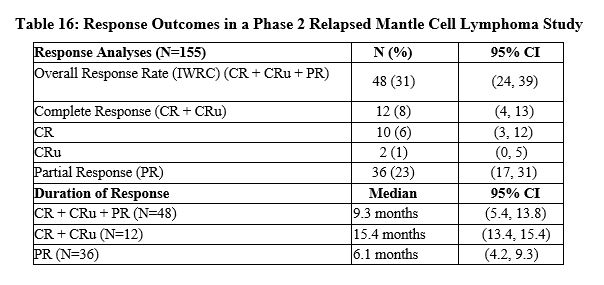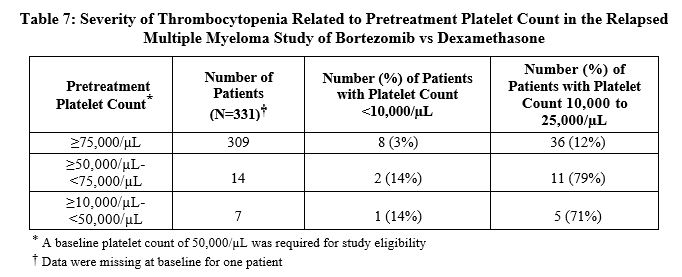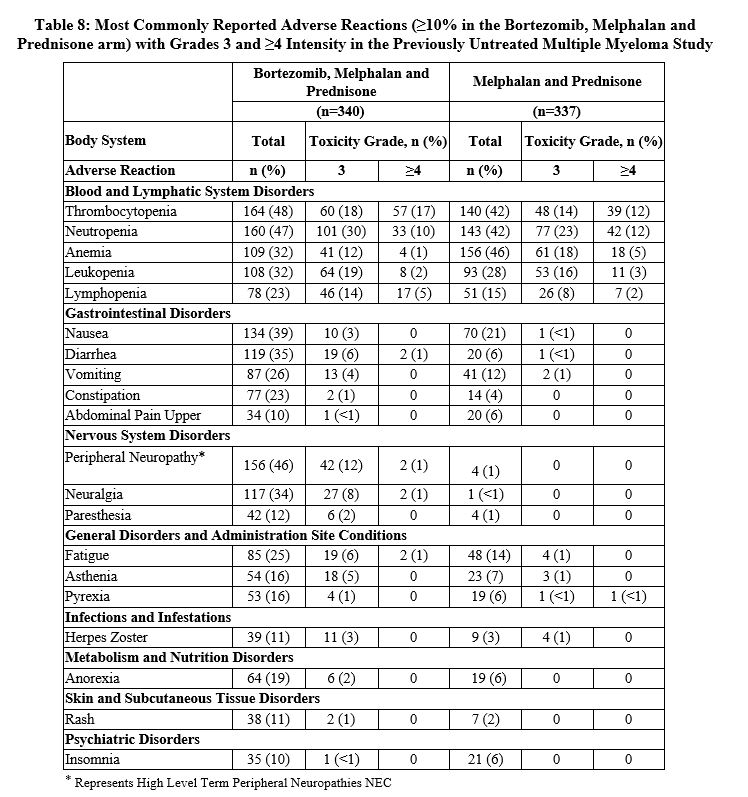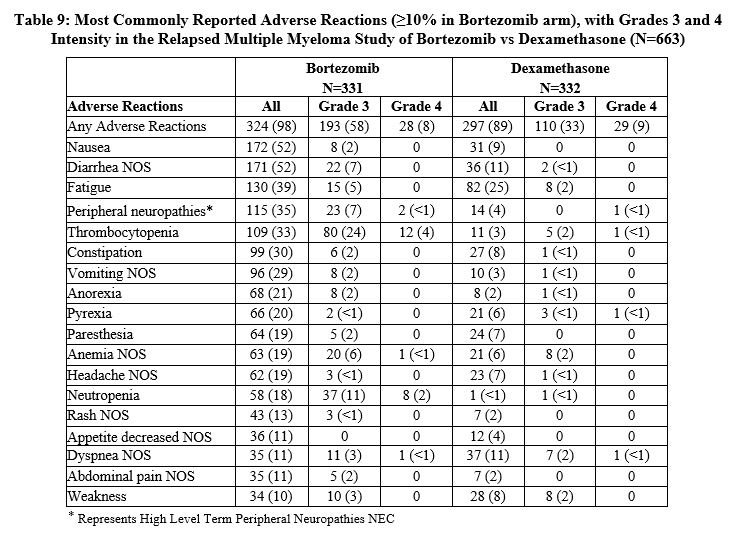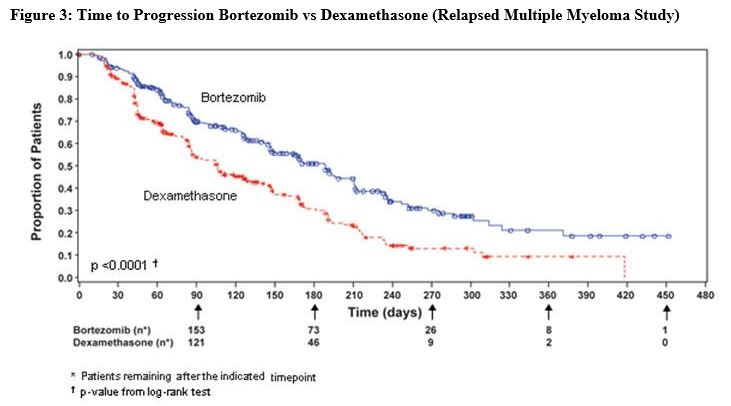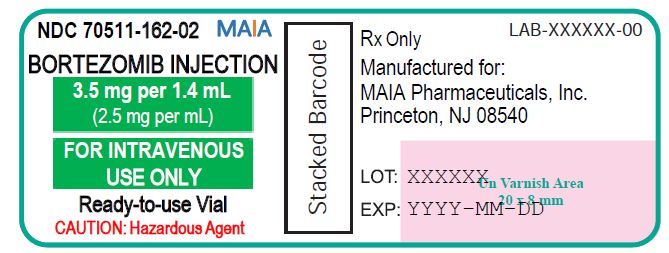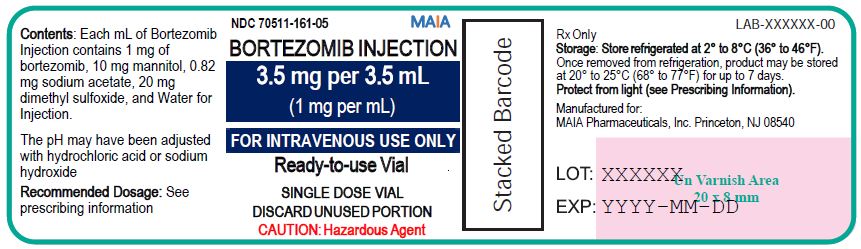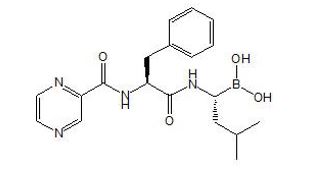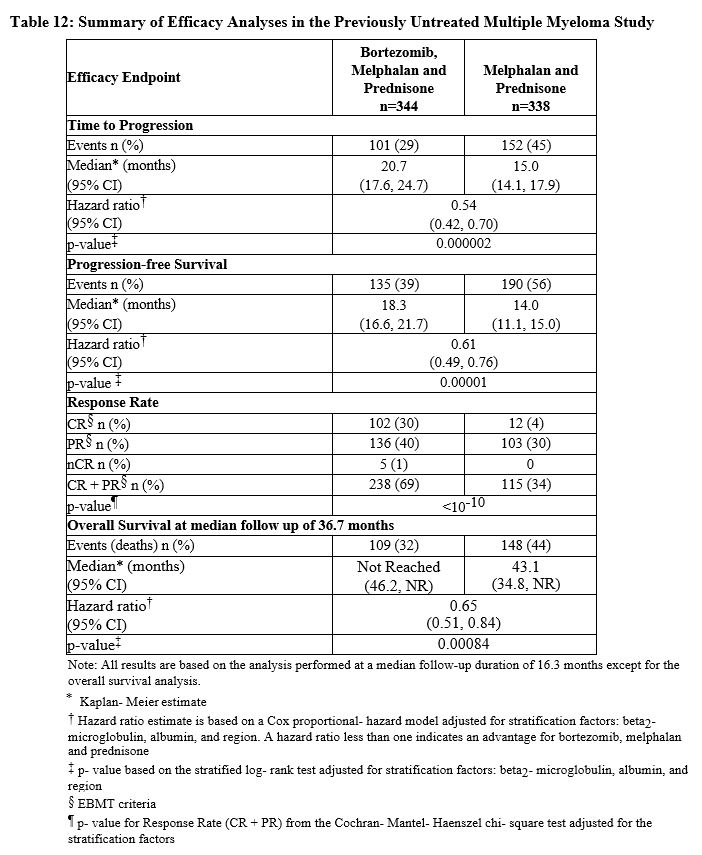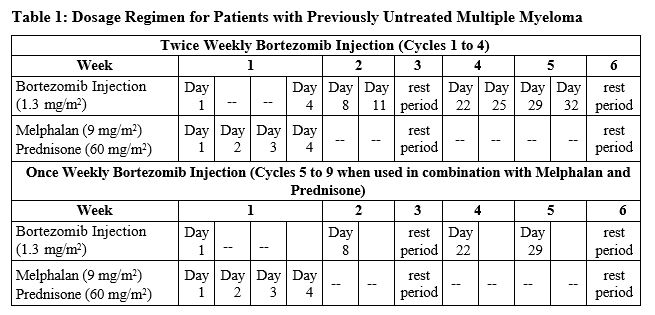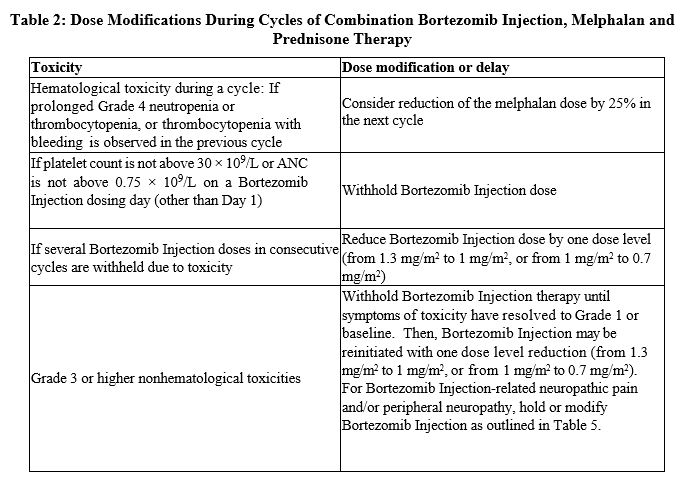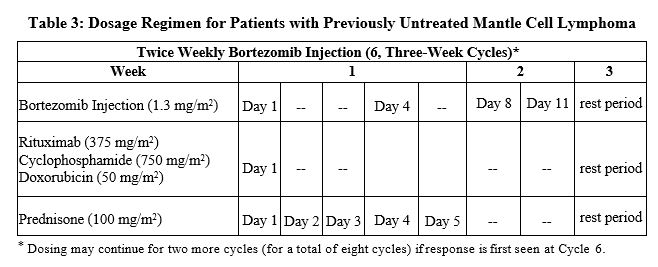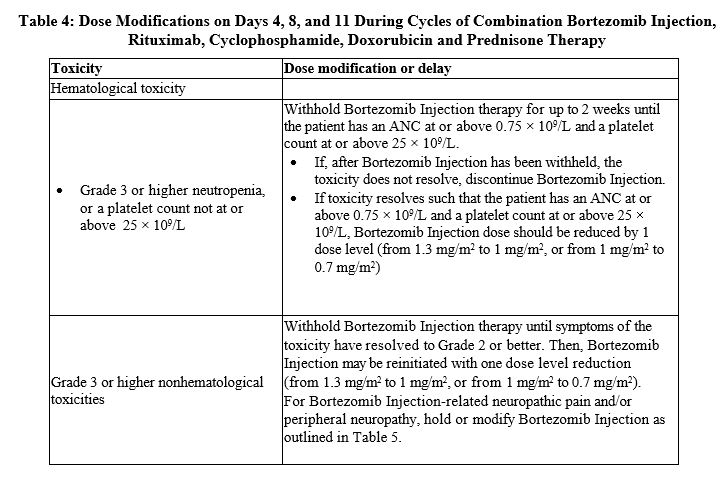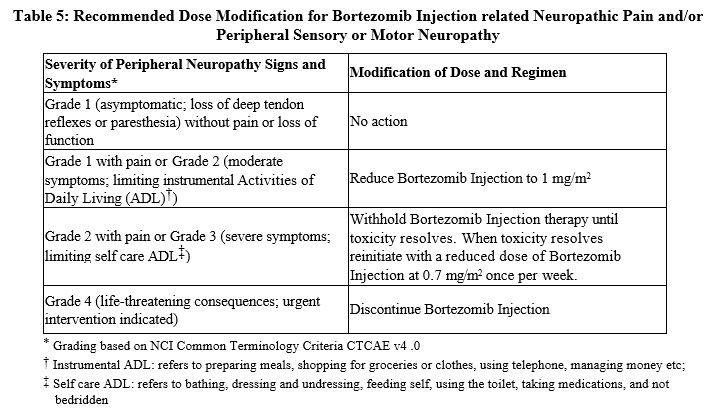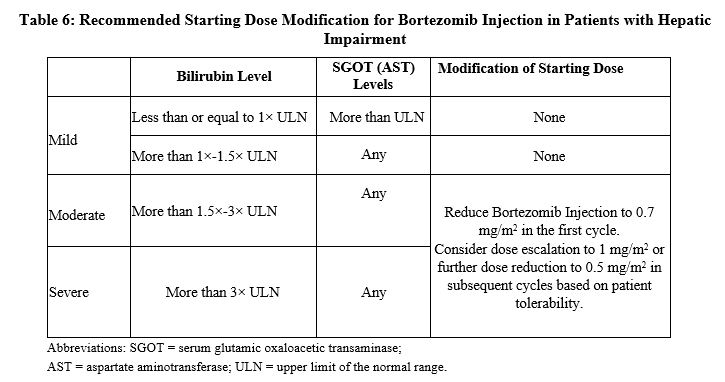 DRUG LABEL: Bortezomib
NDC: 70511-161 | Form: INJECTION
Manufacturer: MAIA Pharmaceuticals, Inc.
Category: prescription | Type: HUMAN PRESCRIPTION DRUG LABEL
Date: 20210922

ACTIVE INGREDIENTS: BORTEZOMIB 1 mg/1 1
INACTIVE INGREDIENTS: MANNITOL 10 mg/1 1; SODIUM ACETATE 0.82 mg/1 1; DIMETHYL SULFOXIDE 20 mg/1 1; HYDROCHLORIC ACID; SODIUM HYDROXIDE

HIGHLIGHTS OF PRESCRIBING INFORMATION

These highlights do not include all the information needed to use BORTEZOMIB INJECTION safely and effectively.See full prescribing information for BORTEZOMIB INJECTION. BORTEZOMIB injection, for intravenous use Initial U.S. Approval: 2003

1 INDICATIONS AND USAGE

Bortezomib injection is a proteasome inhibitor indicated for:

- treatment of adult patients with multiple myeloma (1.1)
- treatment of adult patients with mantle cell lymphoma (1.2)

2 DOSAGE AND ADMINISTRATION

- For intravenous use only. (2.1, 2.10)
- The recommended starting dose of Bortezomib Injection is 1.3 mg/m^2 administered as a 3 to 5 second bolus intravenous injection. (2.2, 2.4, 2.6)
- Retreatment for multiple myeloma: May retreat starting at the last tolerated dose. (2.6)
- Hepatic Impairment: Use a lower starting dose for patients with moderate or severe hepatic impairment. (2.8)
- Dose must be individualized to prevent overdose. (2.10)

3 DOSAGE FORMS AND STRENGTHS

Injection

- 3.5 mg/3.5 mL (1 mg/mL) in a single-dose vial
- 3.5 mg/1.4 mL (2.5 mg/mL) in a single-dose vial

4 CONTRAINDICATIONS

- Patients with hypersensitivity (not including local reactions) to bortezomib, boron, or mannitol, including anaphylactic reactions. (4)
- Contraindicated for intrathecal administration. (4)

5 WARNINGS AND PRECAUTIONS

- Peripheral Neuropathy: Manage with dose modification or discontinuation. (2.7) Patients with preexisting severe neuropathy should be treated with Bortezomib Injection only after careful risk-benefit assessment. (2.7, 5.1)
- Hypotension: Use caution when treating patients taking antihypertensives, with a history of syncope, or with dehydration. (5.2)
- Cardiac Toxicity: Worsening of and development of cardiac failure has occurred. Closely monitor patients with existing heart disease or risk factors for heart disease. (5.3)
- Pulmonary Toxicity: Acute respiratory syndromes have occurred. Monitor closely for new or worsening symptoms and consider interrupting Bortezomib Injection therapy. (5.4)
- Posterior Reversible Encephalopathy Syndrome: Consider MRI imaging for onset of visual or neurological symptoms; discontinue Bortezomib Injection if suspected. (5.5)
- Gastrointestinal Toxicity: Nausea, diarrhea, constipation, and vomiting may require use of antiemetic and antidiarrheal medications or fluid replacement. (5.6)
- Thrombocytopenia and Neutropenia: Monitor complete blood counts regularly throughout treatment. (5.7)
- Tumor Lysis Syndrome: Closely monitor patients with high tumor burden. (5.8)
- Hepatic Toxicity: Monitor hepatic enzymes during treatment. Interrupt Bortezomib Injection therapy to assess reversibility. (5.9)
- Thrombotic Microangiopathy: Monitor for signs and symptoms. Discontinue Bortezomib Injection if suspected. (5.10)
- Embryo-fetal Toxicity: Bortezomib Injection can cause fetal harm. Advise females of reproductive potential and males with female partners of reproductive potential of the potential risk to a fetus and to use effective contraception. (5.11)

6 ADVERSE REACTIONS

Most commonly reported adverse reactions (incidence ≥20%) in clinical studies include nausea, diarrhea, thrombocytopenia, neutropenia, peripheral neuropathy, fatigue, neuralgia, anemia, leukopenia, constipation, vomiting, lymphopenia, rash, pyrexia, and anorexia. (6.1)

To report SUSPECTED ADVERSE REACTIONS, contact MAIA Pharmaceuticals, Inc. at 1-888-877-9064 or FDA at 1-800-FDA-1088 or www.fda.gov/medwatch

7 DRUG INTERACTIONS

- Strong CYP3A4 Inhibitors: Closely monitor patients with concomitant use. (7.1)
- Strong CYP3A4 Inducers: Avoid concomitant use. (7.1)

FULL PRESCRIBING INFORMATION

1 INDICATIONS AND USAGE

1.1 Multiple Myeloma

Bortezomib Injection is indicated for the treatment of adult patients with multiple myeloma.

1.2 Mantle Cell Lymphoma

Bortezomib Injection is indicated for the treatment of adult patients with mantle cell lymphoma.

2 DOSAGE AND ADMINISTRATION

2.1 Important Dosing Guidelines

Bortezomib Injection is a ready-to-use sterile solution for intravenous use only. Do not administer Bortezomib Injection by any other route.

The recommended starting dose of Bortezomib Injection is 1.3 mg/m^2. Bortezomib Injection is administered intravenously at a concentration of 1 mg/mL or 2.5 mg/mL [see Dosage and Administration (2.9 and 2.10)].

Bortezomib Injection retreatment may be considered for patients with multiple myeloma who had previously responded to treatment with bortezomib and who have relapsed at least six months after completing prior bortezomib treatment. Treatment may be started at the last tolerated dose [see Dosage and Administration (2.6)].

Administer Bortezomib Injection as a 3 to 5 second bolus intravenous injection.

2.2 Dosage in Previously Untreated Multiple Myleoma

Bortezomib Injection is administered in combination with oral melphalan and oral prednisone for 9, six-week treatment cycles as shown in Table 1. In Cycles 1 to 4, Bortezomib Injection is administered twice weekly (Days 1, 4, 8, 11, 22, 25, 29 and 32). In Cycles 5 to 9, Bortezomib Injection is administered once weekly (Days 1, 8, 22 and 29). At least 72 hours should elapse between consecutive doses of Bortezomib Injection.

2.3 Dose Modification Guidelines for Bortezomib Injection When Given in Combination with Melphalan and Prednisone

Prior to initiating any cycle of therapy with Bortezomib Injection in combination with melphalan and prednisone:

- Platelet count should be at least 70 × 10^9/L and the absolute neutrophil count (ANC) should be at least 1 × 10^9/L
- Nonhematological toxicities should have resolved to Grade 1 or baseline

For information concerning melphalan and prednisone, see manufacturer's prescribing information.

Dose modifications guidelines for peripheral neuropathy are provided [see Dosage and Administration (2.7)].

2.4 Dosage in Previously Untreated Mantle Cell Lymphoma

Bortezomib Injection (1.3 mg/m^2) is administered intravenously in combination with intravenous rituximab, cyclophosphamide, doxorubicin and oral prednisone (VcR-CAP) for 6, three week treatment cycles as shown in Table 3. Bortezomib Injection is administered first followed by rituximab. Bortezomib Injection is administered twice weekly for two weeks (Days 1, 4, 8, and 11) followed by a ten day rest period on Days 12 to 21. For patients with a response first documented at cycle 6, two additional VcR-CAP cycles are recommended. At least 72 hours should elapse between consecutive doses of Bortezomib Injection.

2.5 Dose Modification Guidelines for Bortezomib Injection When Given in Combination with Rituximab, Cyclophosphamide, Doxorubicin and Prednisone

Prior to the first day of each cycle (other than Cycle 1):

- Platelet count should be at least 100 × 10^9/L and absolute neutrophil count (ANC) should be at least 1.5 × 100^9/L
- Hemoglobin should be at least 8 g/dL (at least 4.96 mmol/L) Nonhematologic toxicity should have recovered to Grade 1 or baseline

Interrupt Bortezomib Injection treatment at the onset of any Grade 3 hematologic or nonhematological toxicities, excluding neuropathy [see Table 5, Warnings and Precautions (5)]. For dose adjustments, see Table 4 below.

For information concerning rituximab, cyclophosphamide, doxorubicin and prednisone, see manufacturer's prescribing information.

2.6 Dosage and Dose Modifications for Relapsed Multiple Myeloma and Relapsed Mantle Cell Lymphoma

Bortezomib Injection (1.3 mg/m^2/dose) is administered twice weekly for two weeks (Days 1, 4, 8, and 11) followed by a ten day rest period (Days 12 to 21). For extended therapy of more than eight cycles, Bortezomib Injection may be administered on the standard schedule or, for relapsed multiple myeloma, on a maintenance schedule of once weekly for four weeks (Days 1, 8, 15, and 22) followed by a 13 day rest period (Days 23 to 35) [see Clinical Studies (14)]. At least 72 hours should elapse between consecutive doses of Bortezomib Injection.

Patients with multiple myeloma who have previously responded to treatment with bortezomib (either alone or in combination) and who have relapsed at least six months after their prior bortezomib therapy may be started on Bortezomib Injection at the last tolerated dose. Retreated patients are administered Bortezomib Injection twice weekly (Days 1, 4, 8, and 11) every three weeks for a maximum of eight cycles. At least 72 hours should elapse between consecutive doses of Bortezomib Injection. Bortezomib Injection may be administered either as a single agent or in combination with dexamethasone [see Clinical Studies (14.1)].

Bortezomib Injection therapy should be withheld at the onset of any Grade 3 nonhematological or Grade 4 hematological toxicities excluding neuropathy as discussed below [see Warnings and Precautions (5)]. Once the symptoms of the toxicity have resolved, Bortezomib Injection therapy may be reinitiated at a 25% reduced dose (1.3 mg/m^2/dose reduced to 1 mg/m^2/dose; 1 mg/m^2/dose reduced to 0.7 mg/m^2/dose).

For dose modifications guidelines for peripheral neuropathy see section 2.7.

2.7 Dose Modifications for Peripheral Neuropathy

Patients with preexisting severe neuropathy should be treated with Bortezomib Injection only after careful risk-benefit assessment.

Patients experiencing new or worsening peripheral neuropathy during Bortezomib Injection therapy may require a decrease in the dose and/or a less dose-intense schedule.

For dose or schedule modification guidelines for patients who experience Bortezomib Injection-related neuropathic pain and/or peripheral neuropathy see Table 5.

2.8 Dosage in Patients with Hepatic Impairment

Do not adjust the starting dose for patients with mild hepatic impairment.

Start patients with moderate or severe hepatic impairment at a reduced dose of 0.7 mg/m^2 per injection during the first cycle, and consider subsequent dose escalation to 1 mg/m^2 or further dose reduction to 0.5 mg/m^2 based on patient tolerance (see Table 6) [see Use in Specific Populations (8.7), Clinical Pharmacology (12.3)].

2.9 Administration Precautions

The drug quantity contained in one vial may exceed the usual dose required. Caution should be used in calculating the dose to prevent overdose [see Dosage and Administration (2.10)].

Bortezomib Injection is a hazardous drug. Follow applicable special handling and disposal procedures.^1

2.10 Instructions for Intravenous Administration

Dose must be individualized to prevent overdosage. After determining patient body surface area (BSA) in square meters, use the following equations to calculate the total volume (mL) of Bortezomib Injection to be administered based on the drug product concentration:

A sticker that indicates the route of administration is provided with each Bortezomib Injection vial. Place this sticker directly on the syringe once the required volume of Bortezomib Injection has been withrdrawn from the vial to help alert the practitioners of the correct route of administration for Bortezomib Injection

Parenteral drug products should be inspected visually for particulate matter and discoloration prior to administration whenever solution and container permit. If any discoloration or particulate matter is observed, the product should not be used. Discard any unused portion.

Stability

Unopened vials of Bortezomib Injection are stable until the date indicated on the package when stored refrigerated at 2 to 8ºC (36 ºF to 46 °F) in the original package protected from light.

Bortezomib Injection contains no antimicrobial preservative. Unopened vials may be stored at room temperature (20ºC to 25ºC [68 ºF to 77 ºF]) for up to 7 days prior to use.

3 DOSAGE FORMS AND STRENGTHS

Injection: Bortezomib Injection is a clear, colorless to slightly yellow sterile solution available as:

- 3.5 mg/3.5 mL (1 mg/mL) in a ready-to-use single-dose vial
- 3.5 mg/1.4 mL (2.5 mg/mL) in a ready-to-use single-dose vial

4 CONTRAINDICATIONS

Bortezomib Injection is contraindicated in patients with hypersensitivity (not including local reactions) to bortezomib, boron, or mannitol. Reactions have included anaphylactic reactions [see Adverse Reactions (6.1)].

Bortezomib Injection is contraindicated for intrathecal administration. Fatal events have occurred with intrathecal administration of bortezomib.

5 WARNINGS AND PRECAUTIONS

5.1 Peripheral Neuropathy

Bortezomib treatment causes a peripheral neuropathy that is predominantly sensory; however, cases of severe sensory and motor peripheral neuropathy have been reported. Patients with preexisting symptoms (numbness, pain or a burning feeling in the feet or hands) and/or signs of peripheral neuropathy may experience worsening peripheral neuropathy (including ≥Grade 3) during treatment with Bortezomib Injection. Patients should be monitored for symptoms of neuropathy, such as a burning sensation, hyperesthesia, hypoesthesia, paresthesia, discomfort, neuropathic pain or weakness. In the Phase 3 relapsed multiple myeloma trial, the incidence of Grade ≥2 peripheral neuropathy was 39% for intravenous administration. Grade ≥3 peripheral neuropathy occurred in 15% of patients in the intravenous treatment group [see Adverse Reactions (6.1)].

Patients experiencing new or worsening peripheral neuropathy during Bortezomib Injection therapy may require a decrease in the dose and/or a less dose-intense schedule [see Dosage and Administration (2.7)]. In the bortezomib vs dexamethasone Phase 3 relapsed multiple myeloma study, improvement in or resolution of peripheral neuropathy was reported in 48% of patients with ≥Grade 2 peripheral neuropathy following dose adjustment or interruption. Improvement in or resolution of peripheral neuropathy was reported in 73% of patients who discontinued due to Grade 2 neuropathy or who had ≥Grade 3 peripheral neuropathy in the Phase 2 multiple myeloma studies. The long- term outcome of peripheral neuropathy has not been studied in mantle cell lymphoma.

5.2 Hypotension

The incidence of hypotension (postural, orthostatic, and hypotension NOS) was 8% [see Adverse Reactions (6.1)]. These events are observed throughout therapy. Patients with a history of syncope, patients receiving medications known to be associated with hypotension, and patients who are dehydrated may be at increased risk of hypotension. Management of orthostatic/postural hypotension may include adjustment of antihypertensive medications, hydration, and administration of mineralocorticoids and/or sympathomimetics.

5.3 Cardiac Toxicity

Acute development or exacerbation of congestive heart failure and new onset of decreased left ventricular ejection fraction have occurred during bortezomib therapy, including reports in patients with no risk factors for decreased left ventricular ejection fraction. [see Adverse Reactions (6.1)] Patients with risk factors for, or existing heart disease should be frequently monitored. In the relapsed multiple myeloma study of bortezomib vs dexamethasone, the incidence of any treatment-related cardiac disorder was 8% and 5% in the bortezomib and dexamethasone groups, respectively. The incidence of adverse reactions suggestive of heart failure (acute pulmonary edema, pulmonary edema, cardiac failure, congestive cardiac failure, cardiogenic shock) was ≤1% for each individual reaction in the bortezomib group. In the dexamethasone group the incidence was ≤1% for cardiac failure and congestive cardiac failure; there were no reported reactions of acute pulmonary edema, pulmonary edema, or cardiogenic shock. There have been isolated cases of QT-interval prolongation in clinical studies; causality has not been established.

5.4 Pulmonary Toxicity

Acute Respiratory Distress Syndrome (ARDS) and acute diffuse infiltrative pulmonary disease of unknown etiology such as pneumonitis, interstitial pneumonia, lung infiltration have occurred in patients receiving bortezomib. Some of these events have been fatal.

In a clinical trial, the first two patients given high-dose cytarabine (2 g/m^2 per day) by continuous infusion with daunorubicin and bortezomib for relapsed acute myelogenous leukemia died of ARDS early in the course of therapy.

There have been reports of pulmonary hypertension associated with bortezomib administration in the absence of left heart failure or significant pulmonary disease.

In the event of new or worsening cardiopulmonary symptoms, consider interrupting Bortezomib Injection until a prompt and comprehensive diagnostic evaluation is conducted

5.5 Posterior Reversible Encephalopathy Syndrome (PRES)

Posterior Reversible Encephalopathy Syndrome (PRES; formerly termed Reversible Posterior Leukoencephalopathy Syndrome (RPLS)) has occurred in patients receiving bortezomib. PRES is a rare, reversible, neurological disorder which can present with seizure, hypertension, headache, lethargy, confusion, blindness, and other visual and neurological disturbances. Brain imaging, preferably MRI (Magnetic Resonance Imaging), is used to confirm the diagnosis. In patients developing PRES, discontinue bortezomib. The safety of reinitiating Bortezomib Injection therapy in patients previously experiencing PRES is not known.

5.6 Gastrointestinal Toxicity

Bortezomib treatment can cause nausea, diarrhea, constipation, and vomiting [see Adverse Reactions (6.1)] sometimes requiring use of antiemetic and antidiarrheal medications. Ileus can occur. Fluid and electrolyte replacement should be administered to prevent dehydration. Interrupt Bortezomib Injection for severe symptoms.

5.7 Thrombocytopenia/Neutropenia

Bortezomib is associated with thrombocytopenia and neutropenia that follow a cyclical pattern with nadirs occurring following the last dose of each cycle and typically recovering prior to initiation of the subsequent cycle. The cyclical pattern of platelet and neutrophil decreases and recovery remain consistent in the studies of multiple myeloma and mantle cell lymphoma, with no evidence of cumulative thrombocytopenia or neutropenia in the treatment regimens studied.

Monitor complete blood counts (CBC) frequently during treatment with Bortezomib Injection. Measure platelet counts prior to each dose of Bortezomib Injection. Adjust dose/schedule for thrombocytopenia [see Tables 2 and 4, Dosage and Administration (2.6)]. Gastrointestinal and intracerebral hemorrhage has occurred during thrombocytopenia in association with bortezomib. Support with transfusions and supportive care, according to published guidelines.

In the single-agent, relapsed multiple myeloma study of bortezomib vs dexamethasone, the mean platelet count nadir measured was approximately 40% of baseline. The severity of thrombocytopenia related to pretreatment platelet count is shown in Table 7. The incidence of bleeding (≥Grade 3) was 2% on the bortezomib arm and was <1% in the dexamethasone arm.

In the combination study of bortezomib with rituximab, cyclophosphamide, doxorubicin and prednisone (VcR-CAP) in previously untreated mantle cell lymphoma patients, the incidence of thrombocytopenia (≥Grade 4) was 32% vs 1% for the rituximab, cyclophosphamide, doxorubicin, vincristine, and prednisone (R-CHOP) arm as shown in Table 12. The incidence of bleeding events (≥Grade 3) was 1.7% in the VcR-CAP arm (four patients) and was 1.2% in the R-CHOP arm (three patients).

Platelet transfusions were given to 23% of the patients in the VcR-CAP arm and 3% of the patients in the R-CHOP arm.

The incidence of neutropenia (≥Grade 4) was 70% in the VcR-CAP arm and was 52% in the R-CHOP arm. The incidence of febrile neutropenia (≥Grade 4) was 5% in the VcR-CAP arm and was 6% in the R-CHOP arm. Myeloid growth factor support was provided at a rate of 78% in the VcR-CAP arm and 61% in the R-CHOP arm.

5.8 Tumor Lysis Syndrome

Tumor lysis syndrome has been reported with bortezomib therapy. Patients at risk of tumor lysis syndrome are those with high tumor burden prior to treatment. Monitor patients closely and take appropriate precautions.

5.9 Hepatic Toxicity

Cases of acute liver failure have been reported in patients receiving multiple concomitant medications and with serious underlying medical conditions. Other reported hepatic reactions include hepatitis, increases in liver enzymes, and hyperbilirubinemia. Interrupt Bortezomib Injection therapy to assess reversibility. There is limited re-challenge information in these patients.

5.10 Thrombotic Microangiopathy

Cases, sometimes fatal, of thrombotic microangiopathy, including thrombotic thrombocytopenic purpura/hemolytic uremic syndrome (TTP/HUS), have been reported in the postmarketing setting in patients who received bortezomib. Monitor for signs and symptoms of TTP/HUS. If the diagnosis is suspected, stop Bortezomib Injection and evaluate. If the diagnosis of TTP/HUS is excluded, consider restarting Bortezomib Injection. The safety of reinitiating Bortezomib Injection therapy in patients previously experiencing TTP/HUS is not known.

5.11 Embryo-fetal Toxicity

Based on the mechanism of action and findings in animals, Bortezomib Injection can cause fetal harm when administered to a pregnant woman. Bortezomib administered to rabbits during organogenesis at a dose approximately 0.5 times the clinical dose of 1.3 mg/m^2 based on body surface area caused postimplantation loss and a decreased number of live fetuses [see Use in Specific Populations (8.1)].

Advise females of reproductive potential that they must use contraception during treatment with Bortezomib Injection and for seven months following treatment. Advise males with female partners of reproductive potential that they must use contraception during treatment with Bortezomib Injection and for four months following treatment. If Bortezomib Injection is used during pregnancy or if the patient becomes pregnant during Bortezomib Injection treatment, the patient should be apprised of the potential risk to the fetus [see Use in Specific Populations (8.1, 8.3), Nonclinical Toxicology (13.1)].

6 ADVERSE REACTIONS

The following clinically significant adverse reactions are also discussed in other sections of the labeling:

- Peripheral Neuropathy [see Warnings and Precautions (5.1)]
- Hypotension [see Warnings and Precautions (5.2)]
- Cardiac Toxicity [see Warnings and Precautions (5.3)] Pulmonary Toxicity [see Warnings and Precautions (5.4)]
- Posterior Reversible Encephalopathy Syndrome (PRES) [see Warnings and Precautions (5.5)]
- Gastrointestinal Toxicity [see Warnings and Precautions (5.6)]
- Thrombocytopenia/Neutropenia [see Warnings and Precautions (5.7)]
- Tumor Lysis Syndrome [see Warnings and Precautions (5.8)]
- Hepatic Toxicity [see Warnings and Precautions (5.9)]
- Thrombotic Microangiopathy [see Warnings and Precautions (5.10)]

6.1 Clinical Trials Experience

Because clinical trials are conducted under widely varying conditions, adverse reaction rates observed in the clinical trials of a drug cannot be directly compared to rates in the clinical trials of another drug and may not reflect the rates observed in clinical practice.

Summary of Clinical Trial in Patients with Previously Untreated Multiple Myeloma

Table 8 describes safety data from 340 patients with previously untreated multiple myeloma who received bortezomib (1.3 mg/m^2) administered intravenously in combination with melphalan (9 mg/m^2) and prednisone (60 mg/m^2) in a prospective randomized study.

The safety profile of Bortezomib Injection in combination with melphalan/prednisone is consistent with the known safety profiles of both bortezomib and melphalan/prednisone

Relapsed Multiple Myeloma Randomized Study of Bortezomib vs Dexamethasone

The safety data described below and in Table 9 reflect exposure to either bortezomib (n=331) or dexamethasone (n=332) in a study of patients with relapsed multiple myeloma. Bortezomib was administered intravenously at doses of 1.3 mg/m^2 twice weekly for two out of three weeks (21 day cycle). After eight 21 day cycles patients continued therapy for three 35 day cycles on a weekly schedule. Duration of treatment was up to 11 cycles (nine months) with a median duration of six cycles (4.1 months). For inclusion in the trial, patients must have had measurable disease and one to three prior therapies. There was no upper age limit for entry. Creatinine clearance could be as low as 20 mL/min and bilirubin levels as high as 1.5 times the upper limit of normal. The overall frequency of adverse reactions was similar in men and women, and in patients <65 and ≥65 years of age. Most patients were Caucasian [see Clinical Studies (14.1)].

Among the 331 bortezomib-treated patients, the most commonly reported (>20%) adverse reactions overall were nausea (52%), diarrhea (52%), fatigue (39%), peripheral neuropathies (35%), thrombocytopenia (33%), constipation (30%), vomiting (29%), and anorexia (21%). The most commonly reported (>20%) adverse reaction reported among the 332 patients in the dexamethasone group was fatigue (25%). Eight percent (8%) of patients in the bortezomib-treated arm experienced a Grade 4 adverse reaction; the most common reactions were thrombocytopenia (4%) and neutropenia (2%). Nine percent (9%) of dexamethasone-treated patients experienced a Grade 4 adverse reaction. All individual dexamethasone-related Grade 4 adverse reactions were less than 1%.

Serious Adverse Reactions and Adverse Reactions Leading to Treatment Discontinuation in the Relapsed Multiple Myeloma Study of Bortezomib vs Dexamethasone

Serious adverse reactions are defined as any reaction that results in death, is life-threatening, requires hospitalization or prolongs a current hospitalization, results in a significant disability, or is deemed to be an important medical event. A total of 80 (24%) patients from the bortezomib treatment arm experienced a serious adverse reaction during the study, as did 83 (25%) dexamethasone-treated patients. The most commonly reported serious adverse reactions in the bortezomib treatment arm were diarrhea (3%), dehydration, herpes zoster, pyrexia, nausea, vomiting, dyspnea, and thrombocytopenia (2% each). In the dexamethasone treatment group, the most commonly reported serious adverse reactions were pneumonia (4%), hyperglycemia (3%), pyrexia, and psychotic disorder (2% each).

A total of 145 patients, including 84 (25%) of 331 patients in the bortezomib treatment group and 61 (18%) of 332 patients in the dexamethasone treatment group were discontinued from treatment due to adverse reactions. Among the 331 bortezomib treated patients, the most commonly reported adverse reaction leading to discontinuation was peripheral neuropathy (8%). Among the 332 patients in the dexamethasone group, the most commonly reported adverse reactions leading to treatment discontinuation were psychotic disorder and hyperglycemia (2% each).

Four deaths were considered to be bortezomib-related in this relapsed multiple myeloma study: one case each of cardiogenic shock, respiratory insufficiency, congestive heart failure and cardiac arrest. Four deaths were considered dexamethasone-related: two cases of sepsis, one case of bacterial meningitis, and one case of sudden death at home.

Most Commonly Reported Adverse Reactions in the Relapsed Multiple Myeloma Study of Bortezomib vs Dexamethasone

The most common adverse reactions from the relapsed multiple myeloma study are shown in Table 9. All adverse reactions with incidence ≥10% in the bortezomib arm are included.

Safety Experience from the Phase 2 Open-Label Extension Study in Relapsed Multiple Myeloma

In the Phase 2 extension study of 63 patients, no new cumulative or new long-term toxicities were observed with prolonged bortezomib treatment. These patients were treated for a total of 5.3 to 23 months, including time on bortezomib in the prior bortezomib study [see Clinical Studies (14.1)].

Safety Experience from the Clinical Trial in Patients with Previously Untreated Mantle Cell Lymphoma

Table 10 describes safety data from 240 patients with previously untreated mantle cell lymphoma who received bortezomib (1.3 mg/m^2) administered intravenously in combination with rituximab (375 mg/m^2), cyclophosphamide (750 mg/m^2), doxorubicin (50 mg/m^2), and prednisone (100 mg/m^2) (VcR-CAP) in a prospective randomized study.

Infections were reported for 31% of patients in the VcR-CAP arm and 23% of the patients in the comparator (rituximab, cyclophosphamide, doxorubicin, vincristine, and prednisone [R-CHOP]) arm, including the predominant preferred term of pneumonia (VcR-CAP 8% vs R-CHOP 5%).

The incidence of herpes zoster reactivation was 4.6% in the VcR-CAP arm and 0.8% in the R-CHOP arm. Antiviral prophylaxis was mandated by protocol amendment.

The incidences of Grade ≥3 bleeding events were similar between the two arms (four patients in the VcR-CAP arm and three patients in the R-CHOP arm). All of the Grade ≥3 bleeding events resolved without sequelae in the VcR-CAP arm.

Adverse reactions leading to discontinuation occurred in 8% of patients in VcR-CAP group and 6% of patients in R-CHOP group. In the VcR-CAP group, the most commonly reported adverse reaction leading to discontinuation was peripheral sensory neuropathy (1%; three patients). The most commonly reported adverse reaction leading to discontinuation in the R-CHOP group was febrile neutropenia (<1%; two patients).

Integrated Summary of Safety (Relapsed Multiple Myeloma and Relapsed Mantle Cell Lymphoma)

Safety data from Phase 2 and 3 studies of single agent bortezomib 1.3 mg/m^2/dose twice weekly for two weeks followed by a ten day rest period in 1163 patients with previously-treated multiple myeloma (N=1008) and previously-treated mantle cell lymphoma (N=155) were integrated and tabulated. In the integrated studies, the safety profile of bortezomib was similar in patients with multiple myeloma and mantle cell lymphoma.

In the integrated analysis, the most commonly reported (>20%) adverse reactions were nausea (49%), diarrhea (46%), asthenic conditions including fatigue (41%) and weakness (11%), peripheral neuropathies (38%), thrombocytopenia (32%), vomiting (28%), constipation (25%), and pyrexia (21%). Eleven percent (11%) of patients experienced at least one episode of ≥Grade 4 toxicity, most commonly thrombocytopenia (4%) and neutropenia (2%).

In the Phase 2 relapsed multiple myeloma clinical trials of bortezomib administered intravenously, local skin irritation was reported in 5% of patients, but extravasation of bortezomib was not associated with tissue damage.

Serious Adverse Reactions and Adverse Reactions Leading to Treatment Discontinuation in the Integrated Summary of Safety

A total of 26% of patients experienced a serious adverse reaction during the studies. The most commonly reported serious adverse reactions included diarrhea, vomiting and pyrexia (3% each), nausea, dehydration, and thrombocytopenia (2% each) and pneumonia, dyspnea, peripheral neuropathies, and herpes zoster (1% each).

Adverse reactions leading to discontinuation occurred in 22% of patients. The reasons for discontinuation included peripheral neuropathy (8%), and fatigue, thrombocytopenia, and diarrhea (2% each).

In total, 2% of the patients died and the cause of death was considered by the investigator to be possibly related to study drug: including reports of cardiac arrest, congestive heart failure, respiratory failure, renal failure, pneumonia and sepsis.

Most Commonly Reported Adverse Reactions in the Integrated Summary of Safety

The most common adverse reactions are shown in Table 11. All adverse reactions occurring at ≥10% are included. In the absence of a randomized comparator arm, it is often not possible to distinguish between adverse events that are drug-caused and those that reflect the patient's underlying disease. Please see the discussion of specific adverse reactions that follows.

Description of Selected Adverse Reactions from the Integrated Phase 2 and 3 Relapsed Multiple Myeloma and Phase 2 Relapsed Mantle Cell Lymphoma Studies

Gastrointestinal Toxicity

A total of 75% of patients experienced at least one gastrointestinal disorder. The most common gastrointestinal disorders included nausea, diarrhea, constipation, vomiting, and appetite decreased. Other gastrointestinal disorders included dyspepsia and dysgeusia. Grade 3 adverse reactions occurred in 14% of patients; ≥Grade 4 adverse reactions were ≤1%. Gastrointestinal adverse reactions were considered serious in 7% of patients. Four percent (4%) of patients discontinued due to a gastrointestinal adverse reaction. Nausea was reported more often in patients with multiple myeloma (51%) compared to patients with mantle cell lymphoma (36%).

Thrombocytopenia

Across the studies, bortezomib-associated thrombocytopenia was characterized by a decrease in platelet count during the dosing period (Days 1 to 11) and a return toward baseline during the ten day rest period during each treatment cycle. Overall, thrombocytopenia was reported in 32% of patients. Thrombocytopenia was Grade 3 in 22%, ≥Grade 4 in 4%, and serious in 2% of patients, and the reaction resulted in bortezomib discontinuation in 2% of patients [see Warnings and Precautions (5.7)].

Thrombocytopenia was reported more often in patients with multiple myeloma (34%) compared to patients with mantle cell lymphoma (16%). The incidence of ≥Grade 3 thrombocytopenia also was higher in patients with multiple myeloma (28%) compared to patients with mantle cell lymphoma (8%).

Peripheral Neuropathy

Overall, peripheral neuropathies occurred in 38% of patients. Peripheral neuropathy was Grade 3 for 11% of patients and ≥Grade 4 for <1% of patients. Eight percent (8%) of patients discontinued bortezomib due to peripheral neuropathy. The incidence of peripheral neuropathy was higher among patients with mantle cell lymphoma (54%) compared to patients with multiple myeloma (36%).

In the bortezomib vs dexamethasone Phase 3 relapsed multiple myeloma study, among the 62 bortezomib-treated patients who experienced ≥Grade 2 peripheral neuropathy and had dose adjustments, 48% had improved or resolved with a median of 3.8 months from first onset.

In the Phase 2 relapsed multiple myeloma studies, among the 30 patients who experienced Grade 2 peripheral neuropathy resulting in discontinuation or who experienced ≥Grade 3 peripheral neuropathy, 73% reported improvement or resolution with a median time of 47 days to improvement of one Grade or more from the last dose of bortezomib.

Hypotension

The incidence of hypotension (postural, orthostatic and hypotension NOS) was 8% in patients treated with bortezomib. Hypotension was Grade 1 or 2 in the majority of patients and Grade 3 in 2% and ≥Grade 4 in <1%. Two percent (2%) of patients had hypotension reported as a serious adverse reaction, and 1% discontinued due to hypotension. The incidence of hypotension was similar in patients with multiple myeloma (8%) and those with mantle cell lymphoma (9%). In addition, <1% of patients experienced hypotension associated with a syncopal reaction.

Neutropenia

Neutrophil counts decreased during the bortezomib dosing period (Days 1 to 11) and returned toward baseline during the ten day rest period during each treatment cycle. Overall, neutropenia occurred in 15% of patients and was Grade 3 in 8% of patients and ≥Grade 4 in 2%. Neutropenia was reported as a serious adverse reaction in <1% of patients and <1% of patients discontinued due to neutropenia. The incidence of neutropenia was higher in patients with multiple myeloma (16%) compared to patients with mantle cell lymphoma (5%). The incidence of ≥Grade 3 neutropenia also was higher in patients with multiple myeloma (12%) compared to patients with mantle cell lymphoma (3%).

Asthenic conditions (Fatigue, Malaise, Weakness, Asthenia)

Asthenic conditions were reported in 54% of patients. Fatigue was reported as Grade 3 in 7% and ≥Grade 4 in <1% of patients. Asthenia was reported as Grade 3 in 2% and ≥Grade 4 in < 1% of patients. Two percent (2%) of patients discontinued treatment due to fatigue and < 1% due to weakness and asthenia. Asthenic conditions were reported in 53% of patients with multiple myeloma and 59% of patients with mantle cell lymphoma.

Pyrexia

Pyrexia (> 38°C) was reported as an adverse reaction for 21% of patients. The reaction was Grade 3 in 1% and ≥Grade 4 in <1%. Pyrexia was reported as a serious adverse reaction in 3% of patients and led to bortezomib discontinuation in <1% of patients. The incidence of pyrexia was higher among patients with multiple myeloma (23%) compared to patients with mantle cell lymphoma (10%). The incidence of ≥Grade 3 pyrexia was 1% in patients with multiple myeloma and <1% in patients with mantle cell lymphoma.

Herpes Virus Infection

Consider using antiviral prophylaxis in subjects being treated with Bortezomib Injection. In the randomized studies in previously untreated and relapsed multiple myeloma, herpes zoster reactivation was more common in subjects treated with bortezomib (ranging between 6 to 11%) than in the control groups (3 to 4%). Herpes simplex was seen in 1 to 3% in subjects treated with bortezomib and 1 to 3% in the control groups. In the previously untreated multiple myeloma study, herpes zoster virus reactivation in the bortezomib, melphalan and prednisone arm was less common in subjects receiving prophylactic antiviral therapy (3%) than in subjects who did not receive prophylactic antiviral therapy (17%).

Retreatment in Relapsed Multiple Myeloma

A single-arm trial was conducted in 130 patients with relapsed multiple myeloma to determine the efficacy and safety of retreatment with intravenous bortezomib. The safety profile of patients in this trial is consistent with the known safety profile of bortezomib-treated patients with relapsed multiple myeloma as demonstrated in Tables 10, 11, and 13; no cumulative toxicities were observed upon retreatment. The most common adverse drug reaction was thrombocytopenia which occurred in 52% of the patients. The incidence of ≥Grade 3 thrombocytopenia was 24%. Peripheral neuropathy occurred in 28% of patients, with the incidence of ≥Grade 3 peripheral neuropathy reported at 6%. The incidence of serious adverse reactions was 12.3%. The most commonly reported serious adverse reactions were thrombocytopenia (3.8%), diarrhea (2.3%), and herpes zoster and pneumonia (1.5% each).

Adverse reactions leading to discontinuation occurred in 13% of patients. The reasons for discontinuation included peripheral neuropathy (5%) and diarrhea (3%).

Two deaths considered to be bortezomib-related occurred within 30 days of the last bortezomib dose; one in a patient with cerebrovascular accident and one in a patient with sepsis.

Additional Adverse Reactions from Clinical Studies

The following clinically important serious adverse reactions that are not described above have been reported in clinical trials in patients treated with bortezomib administered as monotherapy or in combination with other chemotherapeutics. These studies were conducted in patients with hematological malignancies and in solid tumors.

Blood and Lymphatic System Disorders: Anemia, disseminated intravascular coagulation, febrile neutropenia, lymphopenia, leukopenia

Cardiac Disorders: Angina pectoris, atrial fibrillation aggravated, atrial flutter, bradycardia, sinus arrest, cardiac amyloidosis, complete atrioventricular block, myocardial ischemia, myocardial infarction, pericarditis, pericardial effusion, Torsades de pointes, ventricular tachycardia

Ear and Labyrinth Disorders: Hearing impaired, vertigo

Eye Disorders: Diplopia and blurred vision, conjunctival infection, irritation

Gastrointestinal Disorders: Abdominal pain, ascites, dysphagia, fecal impaction, gastroenteritis, gastritis hemorrhagic, hematemesis, hemorrhagic duodenitis, ileus paralytic, large intestinal obstruction, paralytic intestinal obstruction, peritonitis, small intestinal obstruction, large intestinal perforation, stomatitis, melena, pancreatitis acute, oral mucosal petechiae, gastroesophageal reflux

General Disorders and Administration Site Conditions: Chills, edema, edema peripheral, injection site erythema, neuralgia, injection site pain, irritation, malaise, phlebitis

Hepatobiliary Disorders: Cholestasis, hepatic hemorrhage, hyperbilirubinemia, portal vein thrombosis, hepatitis, liver failure

Immune System Disorders: Anaphylactic reaction, drug hypersensitivity, immune complex mediated hypersensitivity, angioedema, laryngeal edema

Infections and Infestations: Aspergillosis, bacteremia, bronchitis, urinary tract infection, herpes viral infection, listeriosis, nasopharyngitis, pneumonia, respiratory tract infection, septic shock, toxoplasmosis, oral candidiasis, sinusitis, catheter related infection

Injury, Poisoning and Procedural Complications: Catheter related complication, skeletal fracture, subdural hematoma

Investigations: Weight decreased

Metabolism and Nutrition Disorders: Dehydration, hypocalcemia, hyperuricemia, hypokalemia, hyperkalemia, hyponatremia, hypernatremia

Musculoskeletal and Connective Tissue Disorders: Arthralgia, back pain, bone pain, myalgia, pain in extremity

Nervous System Disorders: Ataxia, coma, dizziness, dysarthria, dysesthesia, dysautonomia, encephalopathy, cranial palsy, grand mal convulsion, headache, hemorrhagic stroke, motor dysfunction, neuralgia, spinal cord compression, paralysis, postherpetic neuralgia, transient ischemic attack

Psychiatric Disorders: Agitation, anxiety, confusion, insomnia, mental status change, psychotic disorder, suicidal ideation

Renal and Urinary Disorders: Calculus renal, bilateral hydronephrosis, bladder spasm, hematuria, hemorrhagic cystitis, urinary incontinence, urinary retention, renal failure (acute and chronic), glomerular nephritis proliferative

Respiratory, Thoracic and Mediastinal Disorders: Acute respiratory distress syndrome, aspiration pneumonia, atelectasis, chronic obstructive airways disease exacerbated, cough, dysphagia, dyspnea, dyspnea exertional, epistaxis, hemoptysis, hypoxia, lung infiltration, pleural effusion, pneumonitis, respiratory distress, pulmonary hypertension

Skin and Subcutaneous Tissue disorders: Urticaria, face edema, rash (which may be pruritic), leukocytoclastic vasculitis, pruritus.

Vascular Disorders: Cerebrovascular accident, cerebral hemorrhage, deep venous thrombosis, hypertension, peripheral embolism, pulmonary embolism, pulmonary hypertension

6.2 Postmarketing Experience

The following adverse reactions have been identified from the worldwide postmarketing experience with bortezomib. Because these reactions are reported voluntarily from a population of uncertain size, it is not always possible to reliably estimate their frequency or establish a causal relationship to drug exposure:

Cardiac Disorders: Cardiac tamponade

Ear and Labyrinth Disorders: Deafness bilateral

Eye Disorders: Optic neuropathy, blindness, chalazion/blepharitis

Gastrointestinal Disorders: Ischemic colitis

Infections and Infestations: Progressive multifocal leukoencephalopathy (PML), ophthalmic herpes, herpes meningoencephalitis

Nervous System Disorders: Posterior reversible encephalopathy syndrome (PRES, formerly RPLS), Guillain-Barré syndrome, demyelinating polyneuropathy

Respiratory, Thoracic and Mediastinal Disorders: Acute diffuse infiltrative pulmonary disease

Skin and Subcutaneous Tissue Disorders: Stevens-Johnson syndrome/toxic epidermal necrolysis (SJS/TEN), acute febrile neutrophilic dermatosis (Sweet's syndrome)

7 DRUG INTERACTIONS

7.1 Effects of Other Drugs on Bortezomib Injection

Strong CYP3A4 Inducers

Coadministration with a strong CYP3A4 inducer decreases the exposure of bortezomib [see Clinical Pharmacology (12.3)] which may decrease Bortezomib Injection efficacy. Avoid coadministration with strong CYP3A4 inducers.

Strong CYP3A4 Inhibitors

Coadministration with a strong CYP3A4 inhibitor increases the exposure of bortezomib [see Clinical Pharmacology (12.3)] which may increase the risk of Bortezomib Injection toxicities. Monitor patients for signs of bortezomib toxicity and consider a Bortezomib Injection dose reduction if Bortezomib Injection must be given in combination with strong CYP3A4 inhibitors.

7.2 Drugs Without Clinically Significant Interactions with Bortezomib Injection

No clinically significant drug interactions have been observed when bortezomib was coadministered with dexamethasone, omeprazole, or melphalan in combination with prednisone [see Clinical Pharmacology (12.3)].

8 USE IN SPECIFIC POPULATIONS

8.1 Pregnancy

Risk Summary

Based on its mechanism of action [see Clinical Pharmacology (12.1)] and findings in animals, Bortezomib Injection can cause fetal harm when administered to a pregnant woman. There are no studies with the use of bortezomib in pregnant women to inform drug-associated risks. Bortezomib caused embryo-fetal lethality in rabbits at doses lower than the clinical dose (see Data). Advise pregnant women of the potential risk to the fetus.

Adverse outcomes in pregnancy occur regardless of the health of the mother or the use of medications. The estimated background risk of major birth defects and miscarriage for the indicated population is unknown. In the U.S. general population, the estimated background risk of major birth defects and miscarriage in clinically recognized pregnancies is 2 to 4% and 15 to 20%, respectively.

Data

Animal Data

Bortezomib was not teratogenic in nonclinical developmental toxicity studies in rats and rabbits at the highest dose tested (0.075 mg/kg; 0.5 mg/m^2 in the rat and 0.05 mg/kg; 0.6 mg/m^2 in the rabbit) when administered during organogenesis. These dosages are approximately 0.5 times the clinical dose of 1.3 mg/m^2 based on body surface area.

Bortezomib caused embryo-fetal lethality in rabbits at doses lower than the clinical dose (approximately 0.5 times the clinical dose of 1.3 mg/m^2 based on body surface area). Pregnant rabbits given bortezomib during organogenesis at a dose of 0.05 mg/kg (0.6 mg/m^2) experienced significant postimplantation loss and decreased number of live fetuses. Live fetuses from these litters also showed significant decreases in fetal weight.

8.2 Lactation

Risk Summary

There are no data on the presence of bortezomib or its metabolites in human milk, the effects of the drug on the breastfed child, or the effects of the drug on milk production. Because many drugs are excreted in human milk and because the potential for serious adverse reactions in a breastfed child from Bortezomib Injection is unknown, advise nursing women not to breastfeed during treatment with Bortezomib Injection and for two months after treatment.

8.3 Females and Males of Reproductive Potential

Based on its mechanism of action and findings in animals, Bortezomib Injection can cause fetal harm when administered to a pregnant woman [see Use in Specific Populations (8.1)].

Pregnancy Testing

Conduct pregnancy testing in females of reproductive potential prior to initiating Bortezomib Injection treatment.

Contraception

Females

Advise females of reproductive potential to use effective contraception during treatment with Bortezomib Injection and for seven months after the last dose.

Males

Males with female partners of reproductive potential should use effective contraception during treatment with Bortezomib Injection and for four months after the last dose.

Infertility

Based on the mechanism of action and findings in animals, Bortezomib Injection may have an effect on either male or female fertility [see Nonclinical Toxicology (13.1)].

8.4 Pediatric Use

Safety and effectiveness have not been established in pediatric patients.

The activity and safety of bortezomib in combination with intensive reinduction chemotherapy was evaluated in pediatric and young adult patients with lymphoid malignancies (pre-B cell ALL 77%, 16% with T-cell ALL, and 7% T-cell lymphoblastic lymphoma (LL)), all of whom relapsed within 36 months of initial diagnosis in a single-arm multicenter, non-randomized cooperative group trial. An effective reinduction multiagent chemotherapy regimen was administered in three blocks. Block 1 included vincristine, prednisone, doxorubicin and pegaspargase; Block 2 included cyclophosphamide, etoposide and methotrexate; Block 3 included high dose cytosine arabinoside and asparaginase. Bortezomib was administered at a dose of 1.3 mg/m^2 as a bolus intravenous injection on Days 1, 4, 8, and 11 of Block 1 and Days 1, 4, and 8 of Block 2. There were 140 patients with ALL or LL enrolled and evaluated for safety. The median age was ten years (range 1 to 26), 57% were male, 70% were white, 14% were black, 4% were Asian, 2% were American Indian/ Alaska Native, 1% were Pacific Islander.

The activity was evaluated in a pre-specified subset of the first 60 evaluable patients enrolled on the study with pre-B ALL ≤21 years and relapsed <36 months from diagnosis. The complete remission (CR) rate at day 36 was compared to that in a historical control set of patients who had received the identical backbone therapy without bortezomib. There was no evidence that the addition of bortezomib had any impact on the CR rate.

No new safety concerns were observed when bortezomib was added to a chemotherapy backbone regimen as compared with a historical control group in which the backbone regimen was given without bortezomib.

The BSA-normalized clearance of bortezomib in pediatric patients was similar to that observed in adults.

8.5 Geriatric Use

Of the 669 patients enrolled in the relapsed multiple myeloma study, 245 (37%) were 65 years of age or older: 125 (38%) on the bortezomib arm and 120 (36%) on the dexamethasone arm. Median time to progression and median duration of response for patients ≥65 were longer on bortezomib compared to dexamethasone [5.5 mo vs 4.3 mo, and 8.0 mo vs 4.9 mo, respectively]. On the bortezomib arm, 40% (n=46) of evaluable patients aged ≥65 experienced response (CR+PR) vs 18% (n=21) on the dexamethasone arm. The incidence of Grade 3 and 4 events was 64%, 78% and 75% for bortezomib patients ≤50, 51 to 64 and ≥65 years old, respectively [see Adverse Reactions (6.1); Clinical Studies (14.1)].

No overall differences in safety or effectiveness were observed between patients ≥age 65 and younger patients receiving bortezomib; but greater sensitivity of some older individuals cannot be ruled out.

8.6 Renal Impairment

No starting dosage adjustment of Bortezomib Injection is recommended for patients with renal impairment. In patients requiring dialysis, Bortezomib Injection should be administered after the dialysis procedure [see Clinical Pharmacology (12.3)].

8.7 Hepatic Impairment

No starting dosage adjustment of Bortezomib Injection is recommended for patients with mild hepatic impairment (total bilirubin ≤1× ULN and AST > ULN, or total bilirubin >1 to 1.5× ULN and any AST). The exposure of bortezomib is increased in patients with moderate (total bilirubin ≥1.5 to 3× ULN and any AST) and severe (total bilirubin >3× ULN and any AST) hepatic impairment. Reduce the starting dose in patients with moderate or severe hepatic impairment [see Dosage and Administration (2.8), Clinical Pharmacology (12.3)].

8.8 Patients with Diabetes

During clinical trials, hypoglycemia and hyperglycemia were reported in diabetic patients receiving oral hypoglycemics. Patients on oral antidiabetic agents receiving Bortezomib Injection treatment may require close monitoring of their blood glucose levels and adjustment of the dose of their anti-diabetic medication.

10 OVERDOSAGE

There is no known specific antidote for Bortezomib Injection overdosage. In humans, fatal outcomes following the administration of more than twice the recommended therapeutic dose have been reported, which were associated with the acute onset of symptomatic hypotension (5.2) and thrombocytopenia (5.7). In the event of an overdosage, the patient's vital signs should be monitored and appropriate supportive care given.

Studies in monkeys and dogs showed that intravenous bortezomib doses as low as two times the recommended clinical dose on a mg/m^2 basis were associated with increases in heart rate, decreases in contractility, hypotension, and death. In dog studies, a slight increase in the corrected QT interval was observed at doses resulting in death. In monkeys, doses of 3.0 mg/m^2 and greater (approximately twice the recommended clinical dose) resulted in hypotension starting at one hour postadministration, with progression to death in 12 to 14 hours following drug administration.

11 DESCRIPTION

Bortezomib Injection contains bortezomib which is a proteasome inhibitor. Bortezomib is a modified dipeptidyl boronic acid. The chemical name for bortezomib, the monomeric boronic acid, is [(1R)-3-methyl-1-[[(2S)-1-oxo-3-phenyl-2-[(pyrazinylcarbonyl) amino]propyl]amino]butyl] boronic acid.

Bortezomib has the following chemical structure:

The molecular weight is 384.24. The molecular formula is C19H25BN4O4. The solubility of bortezomib, as the monomeric boronic acid, in water is 3.3 to 3.8 mg/mL in a pH range of 2 to 6.5.

Bortezomib Injection is available as a ready-to-use sterile solution for intravenous injection:

- Each mL of the 3.5 mg/3.5 mL (1 mg/mL) strength contains 1 mg of bortezomib, 10 mg mannitol, 0.82 mg sodium acetate, 20 mg dimethyl sulfoxide, in water for injection in a 5 mL single-dose vial. The pH may have been adjusted with hydrochloric acid or sodium hydroxide.
- Each mL of the 3.5 mg/1.4 mg/mL (2.5 mg/mL) strength contains 2.5 mg of bortezomib, 25 mg mannitol, 0.82 mg sodium acetate, 22 mg dimethyl sulfoxide, in water for injection in a 2 mL single-dose vial. The pH may have been adjusted with hydrochloric acid or sodium hydroxide.

12 CLINICAL PHARMACOLOGY

12.1 Mechanism of Action

Bortezomib is a reversible inhibitor of the chymotrypsin-like activity of the 26S proteasome in mammalian cells. The 26S proteasome is a large protein complex that degrades ubiquitinated proteins.

The ubiquitin-proteasome pathway plays an essential role in regulating the intracellular concentration of specific proteins, thereby maintaining homeostasis within cells. Inhibition of the 26S proteasome prevents this targeted proteolysis, which can affect multiple signaling cascades within the cell. This disruption of normal homeostatic mechanisms can lead to cell death. Experiments have demonstrated that bortezomib is cytotoxic to a variety of cancer cell types in vitro. Bortezomib causes a delay in tumor growth in vivo in nonclinical tumor models, including multiple myeloma.

12.2 Pharmacodynamics

Following twice weekly administration of 1 mg/m^2 and 1.3 mg/m^2 bortezomib doses, the maximum inhibition of 20S proteasome activity (relative to baseline) in whole blood was observed five minutes after drug administration. Comparable maximum inhibition of 20S proteasome activity was observed between 1 and 1.3 mg/m^2 doses. Maximal inhibition ranged from 70% to 84% and from 73% to 83% for the 1 mg/m^2 and 1.3 mg/m^2 dose regimens, respectively.

12.3 Pharmacokinetics

Following intravenous administration of 1 mg/m^2 and 1.3 mg/m^2 doses, the mean maximum plasma concentrations of bortezomib (Cmax) after the first dose (Day 1) were 57 and 112 ng/mL, respectively. When administered twice weekly, the mean maximum observed plasma concentrations ranged from 67 to 106 ng/mL for the 1 mg/m^2 dose and 89 to 120 ng/mL for the 1.3 mg/m^2 dose.

Distribution

The mean distribution volume of bortezomib ranged from approximately 498 to 1884 L/m^2 following single- or repeat-dose administration of 1 mg/m^2 or 1.3 mg/m^2 to patients with multiple myeloma. The binding of bortezomib to human plasma proteins averaged 83% over the concentration range of 100 to 1000 ng/mL.

Elimination

The mean elimination half-life of bortezomib upon multiple dosing ranged from 40 to 193 hours after the 1 mg/m^2 dose and 76 to 108 hours after the 1.3 mg/m^2 dose. The mean total body clearances were 102 and 112 L/h following the first dose for doses of 1 mg/m^2 and 1.3 mg/m^2, respectively, and ranged from 15 to 32 L/h following subsequent doses for doses of 1 and 1.3 mg/m^2, respectively.

Metabolism

Bortezomib is primarily oxidatively metabolized to several inactive metabolites in vitro via cytochrome P450 (CYP) enzymes 3A4, CYP2C19, and CYP1A2, and to a lesser extent by CYP2D6 and CYP2C9.

Excretion

The pathways of elimination of bortezomib have not been characterized in humans.

Specific Populations

No clinically significant differences in the pharmacokinetics of bortezomib were observed based on age, sex, or renal impairment (including patients administered bortezomib after dialysis). The effect of race on bortezomib pharmacokinetics is unknown.

Patients with Hepatic Impairment

Following administration of bortezomib doses ranging from 0.5 to 1.3 mg/m^2, mild (total bilirubin ≤1× ULN and AST > ULN, or total bilirubin >1 to 1.5× ULN and any AST) hepatic impairment did not alter dose-normalized bortezomib AUC when compared to patients with normal hepatic function. Dose normalized mean bortezomib AUC increased by approximately 60% in patients with moderate (total bilirubin >1.5 to 3× ULN and any AST) or severe (total bilirubin >3× ULN and any AST) hepatic impairment. A lower starting dose is recommended in patients with moderate or severe hepatic impairment.

Drug Interaction Studies

Clinical Studies

No clinically significant differences in bortezomib pharmacokinetics were observed when coadministered with dexamethasone (weak CYP3A4 inducer), omeprazole (strong CYP2C19 inhibitor), or melphalan in combination with prednisone.

Strong CYP3A4 inhibitor

Coadministration with ketoconazole (strong CYP3A4 inhibitor) increased bortezomib exposure by 35%.

Strong CYP3A4 inducer

Coadministration with rifampin (strong CYP3A4 inducer) decreased bortezomib exposure by approximately 45%.

In Vitro Studies

Bortezomib may inhibit CYP2C19 activity and increase exposure to drugs that are substrates for this enzyme.

13 NONCLINICAL TOXICOLOGY

13.1 Carcinogenesis, Mutagenesis, Impairment of Fertility

Carcinogenicity studies have not been conducted with bortezomib.

Bortezomib showed clastogenic activity (structural chromosomal aberrations) in the in vitro chromosomal aberration assay using Chinese hamster ovary cells. Bortezomib was not genotoxic when tested in the in vitro mutagenicity assay (Ames test) and in vivo micronucleus assay in mice.

Fertility studies with bortezomib were not performed but evaluation of reproductive tissues has been performed in the general toxicity studies. In the six month rat toxicity study, degenerative effects in the ovary were observed at doses ≥0.3 mg/m^2 (one-fourth of the recommended clinical dose), and degenerative changes in the testes occurred at 1.2 mg/m^2.

13.2 Animal Toxicology and/or Pharmacology

Cardiovascular Toxicity

Studies in monkeys showed that administration of dosages approximately twice the recommended clinical dose resulted in heart rate elevations, followed by profound progressive hypotension, bradycardia, and death 12 to 14 hours post dose. Doses ≥1.2 mg/m^2 induced dose-proportional changes in cardiac parameters. Bortezomib has been shown to distribute to most tissues in the body, including the myocardium. In a repeated dosing toxicity study in the monkey, myocardial hemorrhage, inflammation, and necrosis were also observed.

Chronic Administration

In animal studies at a dose and schedule similar to that recommended for patients (twice weekly dosing for two weeks followed by one week rest), toxicities observed included severe anemia and thrombocytopenia, and gastrointestinal, neurological and lymphoid system toxicities. Neurotoxic effects of bortezomib in animal studies included axonal swelling and degeneration in peripheral nerves, dorsal spinal roots, and tracts of the spinal cord. Additionally, multifocal hemorrhage and necrosis in the brain, eye, and heart were observed.

14 CLINICAL STUDIES

14.1 Multiple Myeloma

Randomized, Open-Label Clinical Study in Patients with Previously Untreated Multiple Myeloma

A prospective, international, randomized (1:1), open-label clinical study (NCT00111319) of 682 patients was conducted to determine whether bortezomib administered intravenously (1.3 mg/m^2) in combination with melphalan (9 mg/m^2) and prednisone (60 mg/m^2) resulted in improvement in time to progression (TTP) when compared to melphalan (9 mg/m^2) and prednisone (60 mg/m^2) in patients with previously untreated multiple myeloma. Treatment was administered for a maximum of nine cycles (approximately 54 weeks) and was discontinued early for disease progression or unacceptable toxicity. Antiviral prophylaxis was recommended for patients on the bortezomib study arm.

The median age of the patients in the study was 71 years (48;91), 50% were male, 88% were Caucasian and the median Karnofsky performance status score for the patients was 80 (60;100). Patients had IgG/IgA/Light chain myeloma in 63%/25%/8% instances, a median hemoglobin of 105 g/L (64;165), and a median platelet count of 221,500 /microliter (33,000;587,000).

Efficacy results for the trial are presented in Table 12. At a prespecified interim analysis (with median follow-up of 16.3 months), the combination of bortezomib, melphalan and prednisone therapy resulted in significantly superior results for time to progression, progression-free survival, overall survival and response rate. Further enrollment was halted, and patients receiving melphalan and prednisone were offered bortezomib in addition. A later, prespecified analysis of overall survival (with median follow- up of 36.7 months with a hazard ratio of 0.65, 95% CI: 0.51, 0.84) resulted in a statistically significant survival benefit for the bortezomib, melphalan and prednisone treatment arm despite subsequent therapies including bortezomib based regimens. In an updated analysis of overall survival based on 387 deaths (median follow-up 60.1 months), the median overall survival for the bortezomib, melphalan and prednisone treatment arm was 56.4 months and for the melphalan and prednisone treatment arm was 43.1 months, with a hazard ratio of 0.695 (95% CI: 0.57, 0.85).

TTP was statistically significantly longer on the bortezomib, melphalan and prednisone arm (see Figure 1). (median follow-up 16.3 months)

Overall survival was statistically significantly longer on the bortezomib, melphalan and prednisone arm (see Figure 2). (median follow-up 60.1 months)

Randomized, Clinical Study in Relapsed Multiple Myeloma of Bortezomib vs Dexamethasone

A prospective Phase 3, international, randomized (1:1), stratified, open-label clinical study (NCT00048230) enrolling 669 patients was designed to determine whether bortezomib resulted in improvement in time to progression (TTP) compared to high-dose dexamethasone in patients with progressive multiple myeloma following 1 to 3 prior therapies. Patients considered to be refractory to prior high-dose dexamethasone were excluded as were those with baseline Grade ≥2 peripheral neuropathy or platelet counts <50,000/µL. A total of 627 patients were evaluable for response.

Stratification factors were based on the number of lines of prior therapy the patient had previously received (one previous line vs more than one line of therapy), time of progression relative to prior treatment (progression during or within six months of stopping their most recent therapy vs relapse >6 months after receiving their most recent therapy), and screening beta2-microglobulin levels (≤2.5 mg/L vs >2.5 mg/L).

Baseline patient and disease characteristics are summarized in Table 13.

Patients in the bortezomib treatment group were to receive 8, three week treatment cycles followed by 3, five week treatment cycles of bortezomib. Patients achieving a CR were treated for four cycles beyond first evidence of CR. Within each three week treatment cycle, bortezomib 1.3 mg/m^2/dose alone was administered by intravenous bolus twice weekly for two weeks on Days 1, 4, 8, and 11 followed by a ten day rest period (Days 12 to 21). Within each five week treatment cycle, bortezomib 1.3 mg/m^2/dose alone was administered by intravenous bolus once weekly for four weeks on Days 1, 8, 15, and 22 followed by a 13 day rest period (Days 23 to 35) [see Dosage and Administration (2.2)].

Patients in the dexamethasone treatment group were to receive 4 five week treatment cycles followed by 5, four week treament cycles. Within each five week treatment cycle, dexamethasone 40 mg/day PO was administered once daily on Days 1 to 4, 9 to 12, and 17 to 20 followed by a 15 day rest period (Days 21 to 35). Within each four week treatment cycle, dexamethasone 40 mg/day PO was administered once daily on Days 1 to 4 followed by a 24 day rest period (Days 5 to 28). Patients with documented progressive disease on dexamethasone were offered bortezomib at a standard dose and schedule on a companion study. Following a preplanned interim analysis of time to progression, the dexamethasone arm was halted and all patients randomized to dexamethasone were offered bortezomib, regardless of disease status.

In the bortezomib arm, 34% of patients received at least one bortezomib dose in all eight of the three week cycles of therapy, and 13% received at least one dose in all 11 cycles. The average number of bortezomib doses during the study was 22, with a range of 1 to 44. In the dexamethasone arm, 40% of patients received at least one dose in all four of the five week treatment cycles of therapy, and 6% received at least one dose in all nine cycles.

The time to event analyses and response rates from the relapsed multiple myeloma study are presented in Table 14. Response and progression were assessed using the European Group for Blood and Marrow Transplantation (EBMT) criteria. Complete response (CR) required <5% plasma cells in the marrow, 100% reduction in M-protein, and a negative immunofixation test (IF-). Partial response (PR) requires ≥50% reduction in serum myeloma protein and ≥90% reduction of urine myeloma protein on at least two occasions for a minimum of at least six weeks along with stable bone disease and normal calcium. Near complete response (nCR) was defined as meeting all the criteria for complete response including 100% reduction in M-protein by protein electrophoresis; however, M-protein was still detectable by immunofixation (IF^+).

TTP was statistically significantly longer on the Bortezomib Injection arm (see Figure 3).

As shown in Figure 4 bortezomib had a significant survival advantage relative to dexamethasone (p<0.05). The median follow-up was 8.3 months.

For the 121 patients achieving a response (CR or PR) on the bortezomib arm, the median duration was 8.0 months (95% CI: 6.9, 11.5 months) compared to 5.6 months (95% CI: 4.8, 9.2 months) for the 56 responders on the dexamethasone arm. The response rate was significantly higher on the bortezomib arm regardless of beta2-microglobulin levels at baseline.

A Randomized Phase 2 Dose-Response Study in Relapsed Multiple Myeloma

An open-label, multicenter study randomized 54 patients with multiple myeloma who had progressed or relapsed on or after front-line therapy to receive bortezomib 1 mg/m^2 or 1.3 mg/m^2 intravenous bolus twice weekly for two weeks on Days 1, 4, 8, and 11 followed by a ten day rest period (Days 12 to 21). The median duration of time between diagnosis of multiple myeloma and first dose of bortezomib on this trial was two years, and patients had received a median of one prior line of treatment (median of three prior therapies). A single complete response was seen at each dose. The overall response rates (CR + PR) were 30% (8/27) at 1 mg/m^2 and 38% (10/26) at 1.3 mg/m^2.

A Phase 2 Open-Label Extension Study in Relapsed Multiple Myeloma

Patients from the two Phase 2 studies, who in the investigators' opinion would experience additional clinical benefit, continued to receive bortezomib beyond 8 cycles on an extension study. Sixty-three (63) patients from the Phase 2 multiple myeloma studies were enrolled and received a median of seven additional cycles of bortezomib therapy for a total median of 14 cycles (range 7 to 32). The overall median dosing intensity was the same in both the parent protocol and extension study. Sixty-seven percent (67%) of patients initiated the extension study at the same or higher dose intensity at which they completed the parent protocol, and 89% of patients maintained the standard three week dosing schedule during the extension study. No new cumulative or new long-term toxicities were observed with prolonged bortezomib treatment [see Adverse Reactions (6.1)].

A Single-Arm Trial of Retreatment in Relapsed Multiple Myeloma

A single arm, open-label trial (NCT00431769) was conducted to determine the efficacy and safety of retreatment with bortezomib. One hundred and thirty patients (≥18 years of age) with multiple myeloma who previously had at least partial response on a bortezomib-containing regimen (median of two prior lines of therapy [range 1 to 7]) were retreated upon progression with bortezomib administered intravenously. Patients were excluded from trial participation if they had peripheral neuropathy or neuropathic pain of Grade ≥2. At least six months after prior bortezomib therapy, bortezomib was restarted at the last tolerated dose of 1.3 mg/m^2 (n=93) or ≤1 mg/m^2 (n=37) and given on Days 1, 4, 8 and 11 every three weeks for maximum of eight cycles either as single agent or in combination with dexamethasone in accordance with the standard of care. Dexamethasone was administered in combination with bortezomib to 83 patients in Cycle 1 with an additional 11 patients receiving dexamethasone during the course of bortezomib retreatment cycles.

The primary endpoint was best confirmed response to retreatment as assessed by European Group for Blood and Marrow Transplantation (EBMT) criteria. Fifty of the 130 patients achieved a best confirmed response of Partial Response or better for an overall response rate of 38.5% (95% CI: 30.1, 47.4). One patient achieved a Complete Response and 49 achieved Partial Response. In the 50 responding patients, the median duration of response was 6.5 months and the range was 0.6 to 19.3 months.

14.2 Mantle Cell Lymphoma

A Randomized, Open-Label Clinical Study in Patients with Previously Untreated Mantle Cell Lymphoma

A randomized, open-label, Phase 3 study (NCT00722137) was conducted in 487 adult patients with previously untreated mantle cell lymphoma (Stage II, III or IV) who were ineligible or not considered for bone marrow transplantation to determine whether bortezomib administered in combination with rituximab, cyclophosphamide, doxorubicin, and prednisone (VcR-CAP) resulted in improvement in progression free survival (PFS) when compared to the combination of rituximab, cyclophosphamide, doxorubicin, vincristine, and prednisone (R-CHOP). This clinical study utilized independent pathology confirmation and independent radiologic response assessment.

Patients in the VcR-CAP treatment arm received bortezomib (1.3 mg/m^2) administered intravenously on Days 1, 4, 8, and 11 (rest period days 12 to 21); rituximab (375 mg/m^2) on Day 1; cyclophosphamide (750 mg/m^2) on Day 1; doxorubicin (50 mg/m^2) on Day 1; and prednisone (100 mg/m^2) on Day 1 through Day 5 of the 21 day treatment cycle. For patients with a response first documented at Cycle six, two additional treatment cycles were allowed.

Median patient age was 66 years, 74% were male, 66% were Caucasian and 32% were Asian. Sixty nine percent of patients had a positive bone marrow aspirate and/or a positive bone marrow biopsy for MCL, 54% of patients had an International Prognostic Index (IPI) score of three (high-intermediate) or higher and 76% had Stage IV disease.

The majority of the patients in both groups received six or more cycles of treatment, 84% in the VcR- CAP group and 83% in the R-CHOP group. Median number of cycles received by patients in both treatment arms was six with 17% of patients in the R-CHOP group and 14% of subjects in the VcR-CAP group receiving up to two additional cycles.

The efficacy results for PFS, CR and ORR with a median follow-up of 40 months are presented in Table 15. The response criteria used to assess efficacy were based on the International Workshop to Standardize Response Criteria for Non-Hodgkin's Lymphoma (IWRC). Final overall survival results at a median follow up of 78.5 months are also presented in Table 15 and Figure 6. The combination of VcR- CAP resulted in statistically significant prolongation of PFS compared with R-CHOP (see Table 18, Figure 5).

Key: R-CHOP=rituximab, cyclophosphamide, doxorubicin, vincristine, and prednisone; VcR- CAP=bortezomib, rituximab, cyclophosphamide, doxorubicin, and prednisone

Key: R-CHOP=rituximab, cyclophosphamide, doxorubicin, vincristine, and prednisone; VcR-CAP= bortezomib, rituximab, cyclophosphamide, doxorubicin, and prednisone.

A Phase 2 Single-arm Clinical Study in Relapsed Mantle Cell Lymphoma After Prior Therapy

The safety and efficacy of bortezomib in relapsed or refractory mantle cell lymphoma were evaluated in an open-label, single-arm, multicenter study (NCT00063713) of 155 patients with progressive disease who had received at least one prior therapy. The median age of the patients was 65 years (42, 89), 81% were male, and 92% were Caucasian. Of the total, 75% had one or more extra-nodal sites of disease, and 77% were Stage 4. In 91% of the patients, prior therapy included all of the following: an anthracycline or mitoxantrone, cyclophosphamide, and rituximab. A total of thirty seven percent (37%) of patients were refractory to their last prior therapy. An intravenous bolus injection of bortezomib 1.3 mg/m^2/dose was administered twice weekly for two weeks on Days 1, 4, 8, and 11 followed by a ten day rest period (Days 12 to 21) for a maximum of 17 treatment cycles. Patients achieving a CR or CRu were treated for four cycles beyond first evidence of CR or CRu. The study employed dose modifications for toxicity [see Dosage and Administration (2.6, 2.7)].

Responses to bortezomib are shown in Table 19. Response rates to bortezomib were determined according to the International Workshop Response Criteria (IWRC) based on independent radiologic review of CT scans. The median number of cycles administered across all patients was four; in responding patients the median number of cycles was eight. The median time to response was 40 days (range 31 to 204 days). The median duration of follow-up was more than 13 months.

15 REFERENCES

1. "OSHA Hazardous Drugs" OSHA. http://www.osha.gov/SLTC/hazardousdrugs/index.html

16 HOW SUPPLIED/STORAGE AND HANDLING

Bortezomib Injection is a clear, colorless to slightly yellow ready-to-use, sterile solution supplied as individually cartoned 5 mL vials containing 3.5 mg/3.5 mL (1 mg/mL) or 2 mL vials containing 3.5 mg/1.4 mL (2.5 mg/mL) of Bortezomib Injection.

3.5 mg/3.5 mL (1mg/mL) in a single-dose 5 mL vial

NDC 70511-161-05

3.5 mg/1.4 mL (2.5 mg/mL) in a single-dose 2 mL vial

NDC 70511-162-02

Store Bortezomib Injection in a refrigerator at 2º to 8°C (36° to 46°F) in the original package to protect from light.

Follow guidelines for handling and disposal for hazardous drugs, including the use of gloves and other protective clothing to prevent skin contact^1.

17 PATIENT COUNSELING INFORMATION

Discuss the following with patients prior to treatment with Bortezomib Injection:

Peripheral Neuropathy

Advise patients to report the development or worsening of sensory and motor peripheral neuropathy to their healthcare provider [see Warnings and Precautions (5.1)].

Hypotension

Advise patients to drink adequate fluids to avoid dehydration and to report symptoms of hypotension to their healthcare provider [see Warnings and Precautions (5.2)].

Instruct patients to seek medical advice if they experience symptoms of dizziness, light headedness or fainting spells, or muscle cramps.

Cardiac Toxicity

Advise patients to report signs or symptoms of heart failure to their healthcare provider [see Warnings and Precautions (5.3)].

Pulmonary Toxicity

Advise patients to report symptoms of ARDS, pulmonary hypertension, pneumonitis, and pneumonia immediately to their healthcare provider [see Warnings and Precautions (5.4)].

Posterior Reversible Encephalopathy Syndrome (PRES)

Advise patients to seek immediate medical attention for signs or symptoms of PRES [see Warnings and Precautions (5.5)].

Gastrointestinal Toxicity

Advise patients to report symptoms of gastrointestinal toxicity to their healthcare provider and to drink adequate fluids to avoid dehydration. Instruct patients to seek medical advice if they experience symptoms of dizziness, light headedness or fainting spells, or muscle cramps [see Warnings and Precautions (5.6)].

Thrombocytopenia/Neutropenia

Advise patients to report signs or symptoms of bleeding or infection immediately to their healthcare provider [see Warnings and Precautions (5.7)].

Tumor Lysis Syndrome

Advise patients of the risk of tumor lysis syndrome and to drink adequate fluids to avoid dehydration

[see Warnings and Precautions (5.8)].

Hepatic Toxicity

Advise patients to report signs or symptoms of hepatic toxicity to their healthcare provider [see Warnings and Precautions (5.9)].

Thrombotic Microangiopathy

Advise patients to seek immediate medical attention if any signs or symptoms of thrombotic microangiopathy occur [see Warnings and Precautions (5.10)].

Ability to Drive or Operate Machinery or Impairment of Mental Ability

Bortezomib Injection may cause fatigue, dizziness, syncope, orthostatic/postural hypotension. Advise patients not to drive or operate machinery if they experience any of these symptoms [see Warnings and Precautions (5.2, 5.5)].

Embryo-fetal Toxicity

Advise females of the potential risk to the fetus and to avoid pregnancy and use effective contraception during treatment with Bortezomib Injection and for seven months following the last dose. Advise male patients with female partners of reproductive potential to use effective contraception during treatment with Bortezomib Injection and for four months following the last dose. Instruct patients to report pregnancy to their physicians immediately if they or their female partner becomes pregnant during treatment or within seven months following last dose [see Warnings and Precautions (5.11)].

Lactation

Advise patients to avoid breastfeeding while receiving Bortezomib Injection and for two months after last dose [see Use in Specific Populations (8.2)].

Concomitant Medications

Advise patients to speak with their physicians about any other medication they are currently taking.

Diabetic Patients

Advise patients to check their blood sugar frequently if using an oral antidiabetic medication and to notify their physicians of any changes in blood sugar level.

Dermal

Advise patients to contact their physicians if they experience rash, severe injection site reactions [see Dosage and Administration (2.9)], or skin pain. Discuss with patients the option for antiviral prophylaxis for herpes virus infection [see Adverse Reactions (6.1)].

Other

Instruct patients to contact their physicians if they develop an increase in blood pressure, bleeding, fever, constipation, or decreased appetite.

Distributed and Marketed by:

MAIA Pharmaceuticals, Inc. 707 State Road,

Suite 104

Princeton, NJ 08540

Made in India - 530049

Principal Display Panel

NDC 70511-161-05 MAIA

BORTEZOMIB (bortezomib) INJECTION

3.5 mg per 3.5 mL

(1 mg per mL)

FOR INTRAVENOUS USE ONLY

READY-to-use Vial

SINGLE DOSE VIAL

DISCARD UNUSED PORTION

CAUTION: Hazardous Agent

NDC 70511-162-02 MAIA

BORTEZOMIB (bortezomib) INJECTION

3.5 mg per 1.4 mL

(2.5 mg per mL)

FOR INTRAVENOUS USE ONLY

Ready-to-use Vial

CAUTION: Hazardous Agent